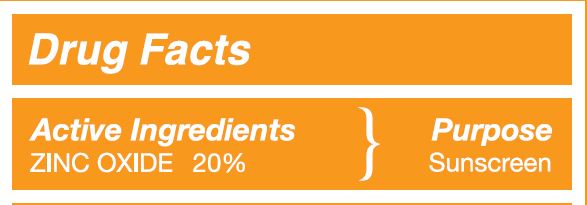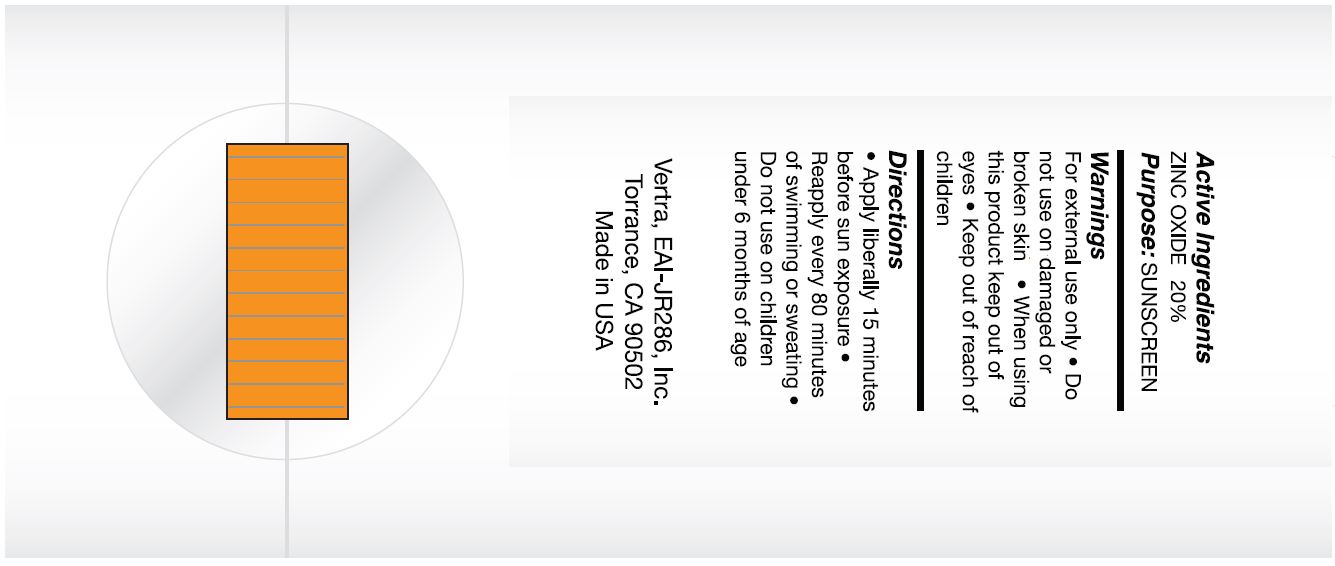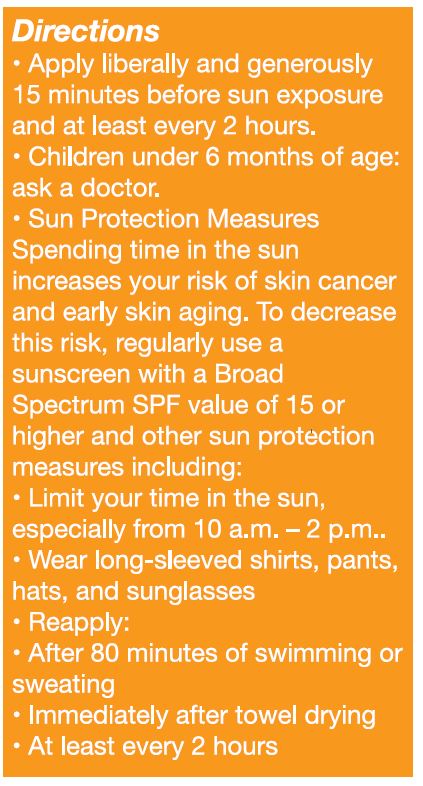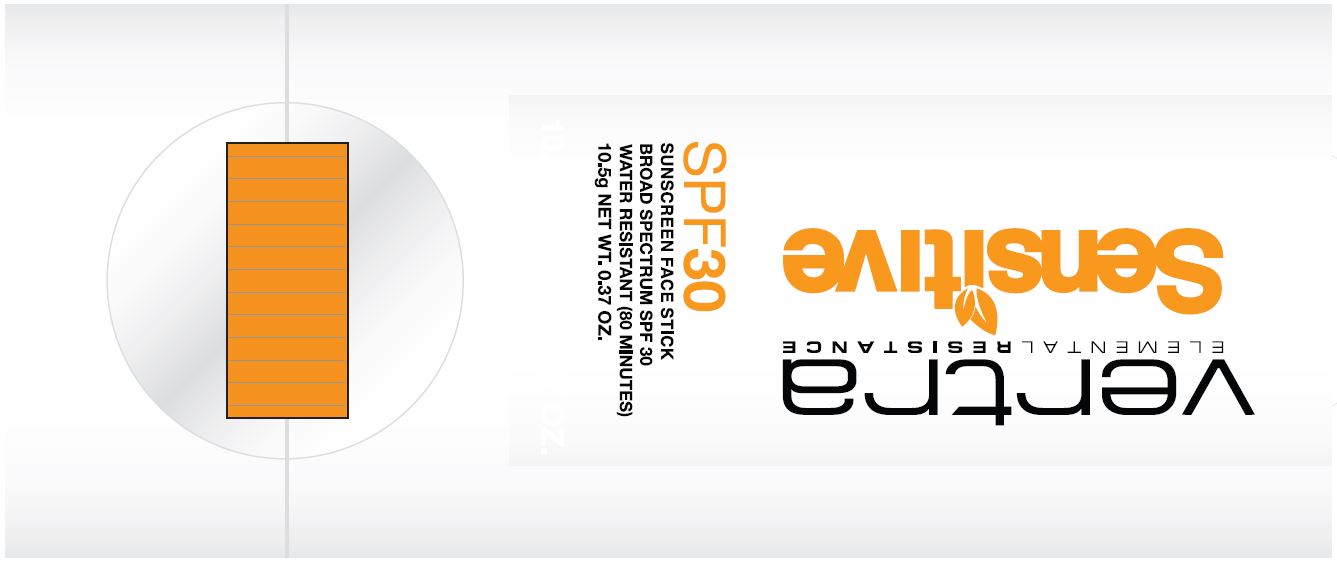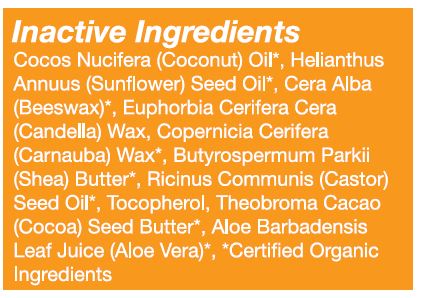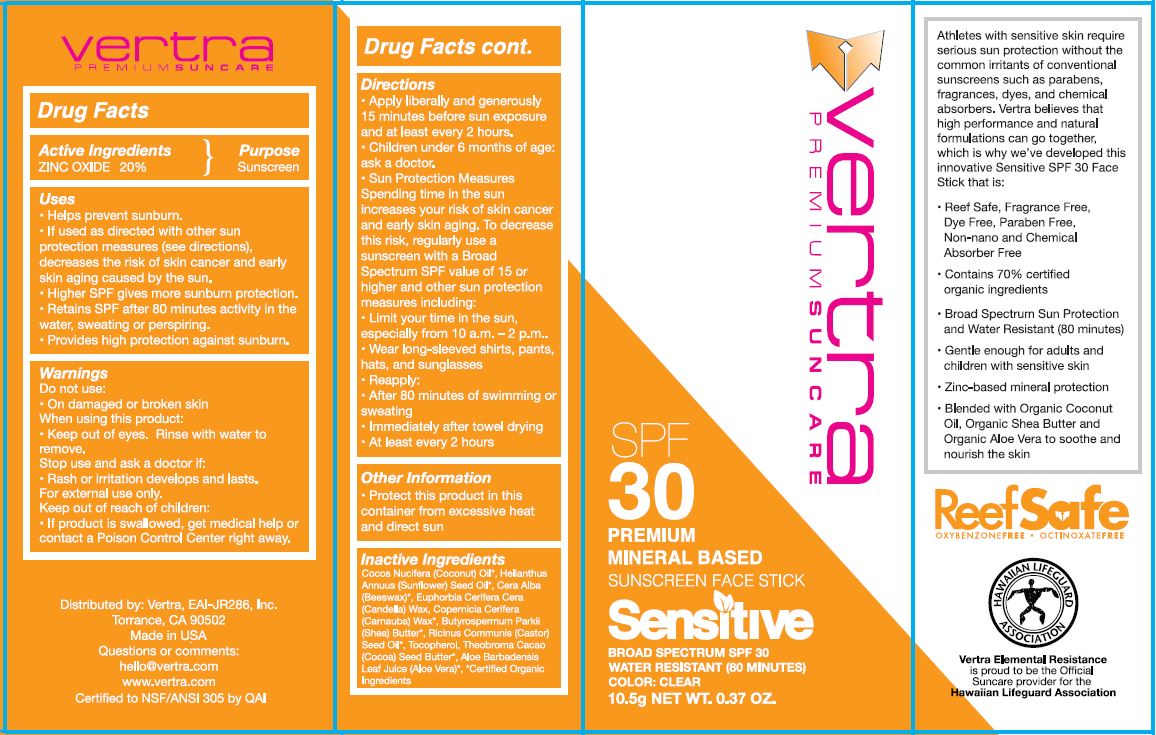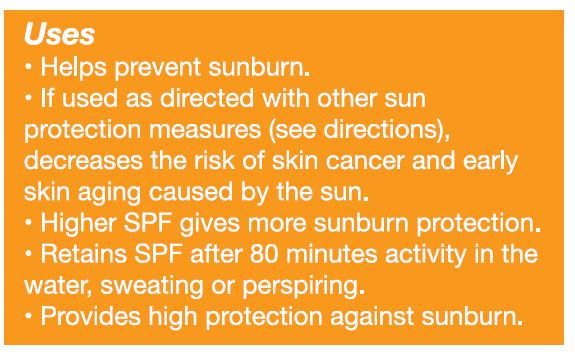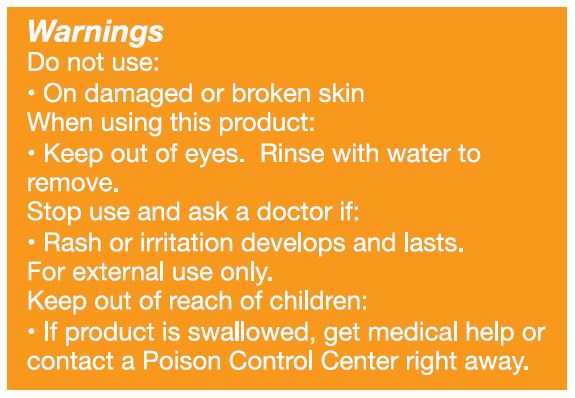 DRUG LABEL: EAI-JR286, Inc Vertra Sensitive SPF 30 Sunscreen Face Stick
NDC: 62932-263 | Form: STICK
Manufacturer: Private Label Select Ltd CO
Category: otc | Type: HUMAN OTC DRUG LABEL
Date: 20220301

ACTIVE INGREDIENTS: ZINC OXIDE 20 g/100 g
INACTIVE INGREDIENTS: WHITE WAX; COCOA BUTTER; CASTOR OIL; SUNFLOWER OIL; CANDELILLA WAX; SHEA BUTTER; COCONUT OIL; .GAMMA.-TOCOPHEROL; .DELTA.-TOCOPHEROL; CARNAUBA WAX; .ALPHA.-TOCOPHEROL, D-; ALOE VERA LEAF; .BETA.-TOCOPHEROL

EAI-JR286, Inc Vertra Sensitive SPF 30 Sunscreen Face Stick